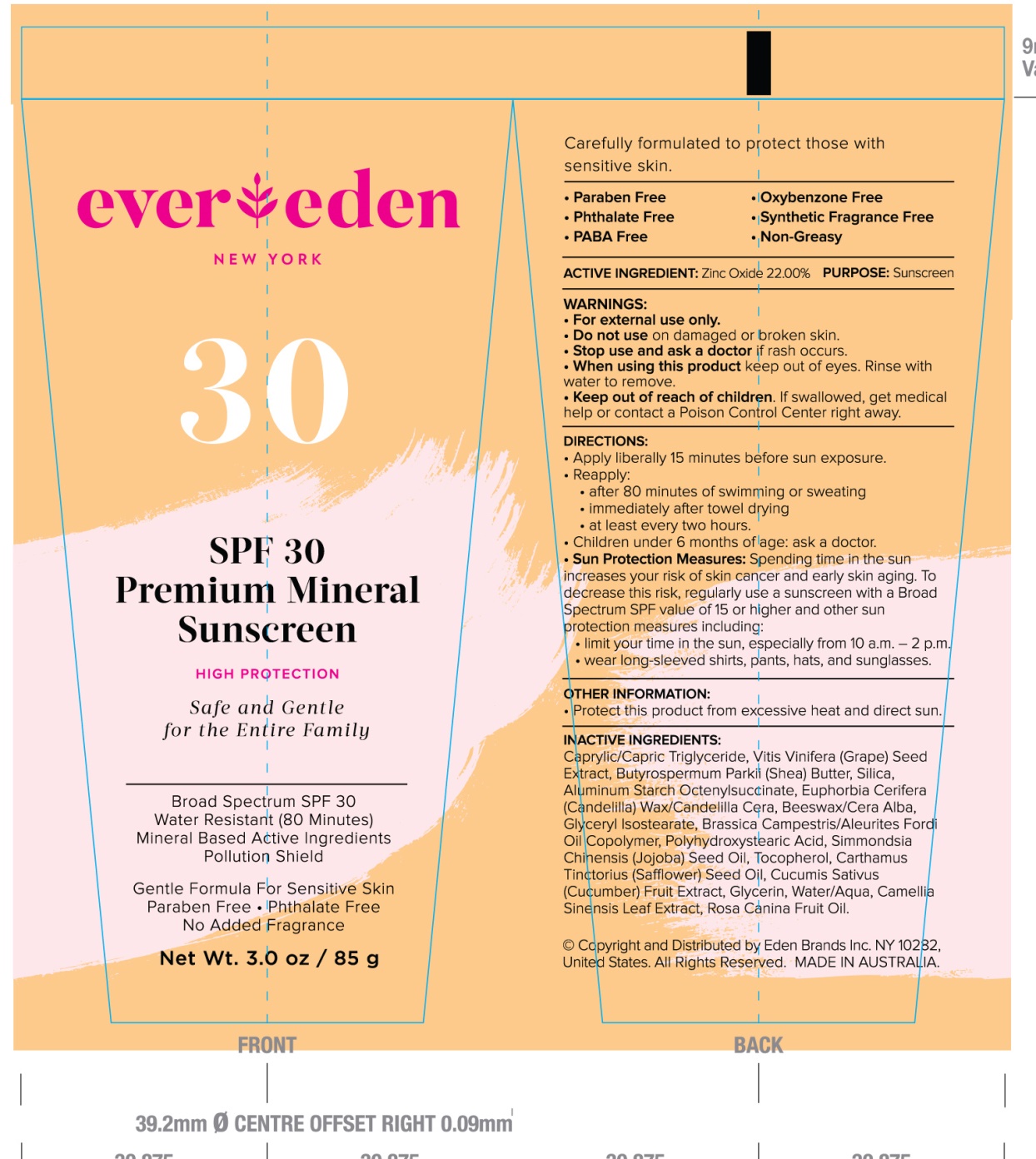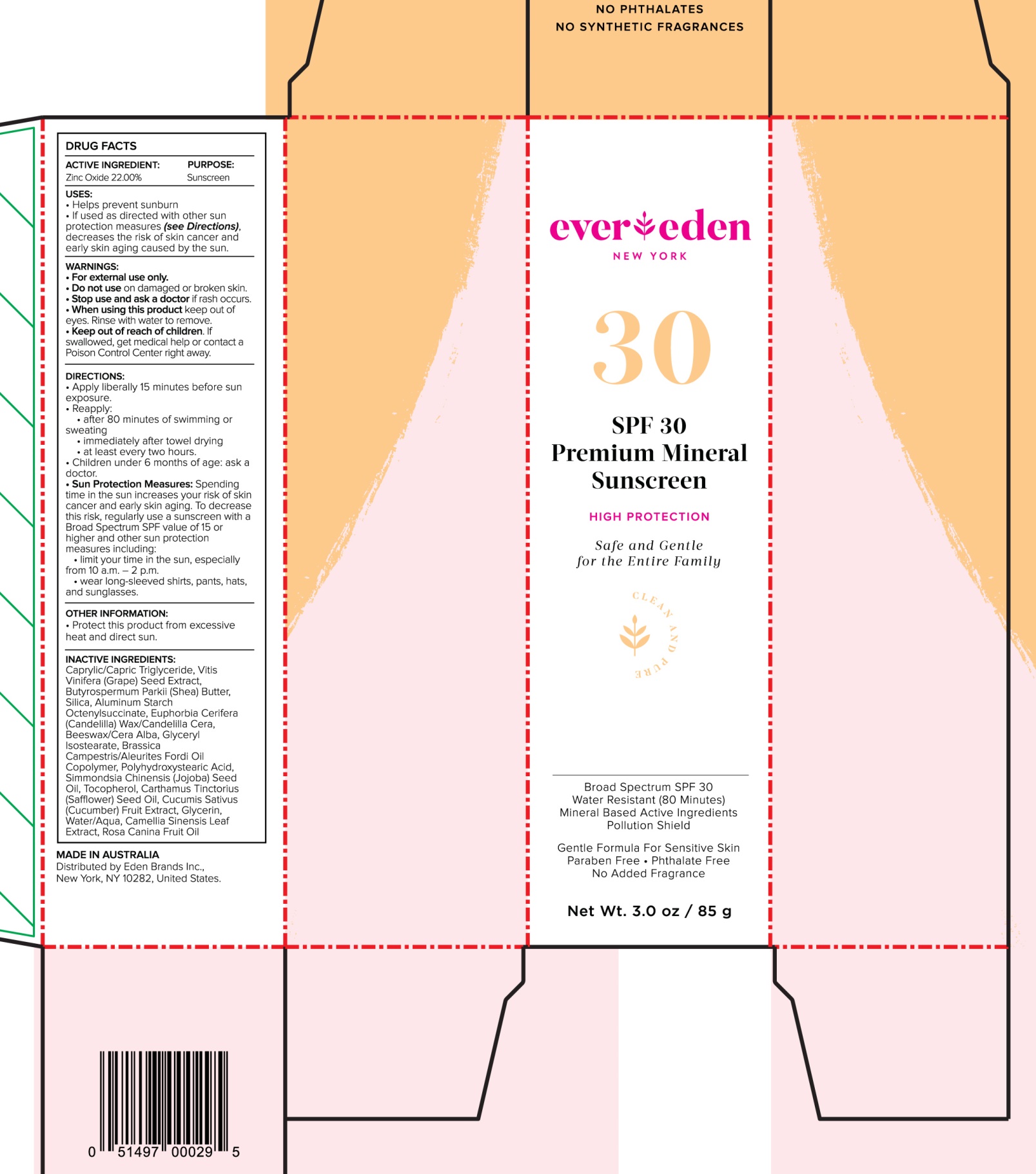 DRUG LABEL: Premium Mineral Sunscreen Broad Spectrum SPF 30
NDC: 72113-101 | Form: LOTION
Manufacturer: Eden Brands
Category: otc | Type: HUMAN OTC DRUG LABEL
Date: 20180212

ACTIVE INGREDIENTS: ZINC OXIDE 22 g/100 g
INACTIVE INGREDIENTS: WATER; WHITE WAX; GLYCERYL ISOSTEARATE; POLYHYDROXYSTEARIC ACID (2300 MW); CUCUMBER; GREEN TEA LEAF; SAFFLOWER OIL; SHEA BUTTER; MEDIUM-CHAIN TRIGLYCERIDES; VITIS VINIFERA SEED; GLYCERIN; ROSA CANINA FRUIT OIL; ALUMINUM STARCH OCTENYLSUCCINATE; CANDELILLA WAX; JOJOBA OIL; TOCOPHEROL

Premium Mineral Sunscreen Broad Spectrum SPF 30

Active ingredients Purpose

Zinc Oxide 22% Sunscreen

Uses

- Helps prevent Sunburn
- If used as directed with other sun protection measures (see Directions), decreases the risk of skin cancer and early skin aging caused by the sun

Keep out of reach of children. If swallowed, get medical help or contact a poison control center right away.

Stop use and ask a doctor if rash occurs.

Warnings:

For external use only.

Do not use on damaged or broken skin.

When using this product keep out of eyes. Rinse with water to remove.

Directions:

- Apply liberally 15 minutes before sun exposure
- Reapply:
  - after 80 minutes of swimming or sweating
  - Immediately after towel drying
  - at least every two hours
  - Children under 6 months of age: ask a doctor
  - Sun Protection Measures: Spending time in the sun increases your risk of cancer and early skin aging. To decrease this risk, regularly use a sunscreen with a Broad Spectrum SPF value of 15 or higher and other sun protection measures including:
  - limit your time in the sun, especially from 10a.m.-2 p.m.
  - Wear long-sleeved shirts, pants, hats, and sunglasses

Inactive ingredients:

Caprylic/Capric Triglyceride, Vitis Vinifera (grape) Seed Extract, Butyrospermum Parkii (shea) Butter, Silica, Aluminum Starch Octenylsuccinate, Euphorbia Cerifera (Candelilla) Wax/Candelilla Cera, Beeswax/Cera Alba, Glyceryl Isostearate, Brassica Campestris/Aleurites Fordii Oil Copolymer, Polyhydroxystearic Acid, Simmondsia Chinensis (jojoba) Seed Oil, Tocopherol, Carthamus Tinctorious (Safflower) Seed Oil, Cucumis Sativus (Cucumber) Fruit Extract, Glycerin, Water/Aqua, Camelilla sinensis leaf Extract, Rosa Canina Fruit Oil.

PACKAGE LABEL

SPF 30 Premium Mineral Sunsreen

High Protection

Broad Spectrum SPF 30

Water resistant (80 minutes)

Mineral based Active Ingredient

Net Wt. 3.0oz / 85 g